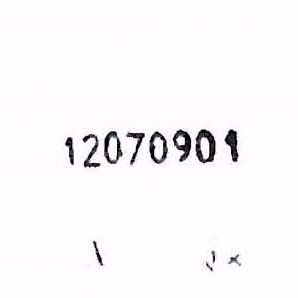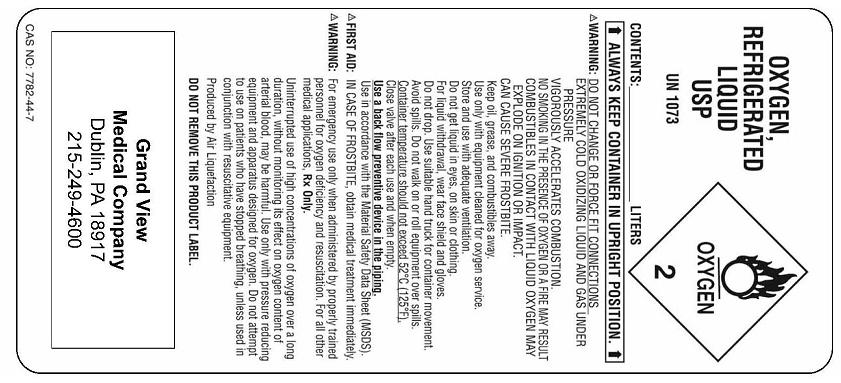 DRUG LABEL: Oxygen
NDC: 59139-0002 | Form: GAS
Manufacturer: Grandview Hospital DBA Grandview Medical Company
Category: prescription | Type: HUMAN PRESCRIPTION DRUG LABEL
Date: 20091215

ACTIVE INGREDIENTS: Oxygen 99 L/100 L

Oxygen